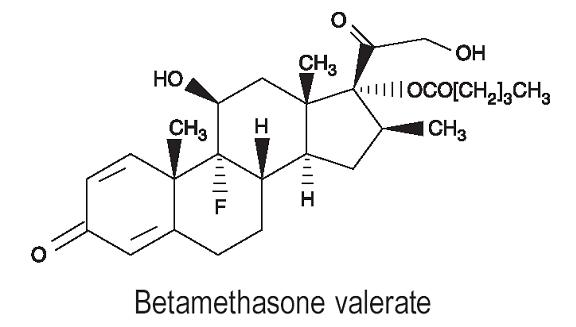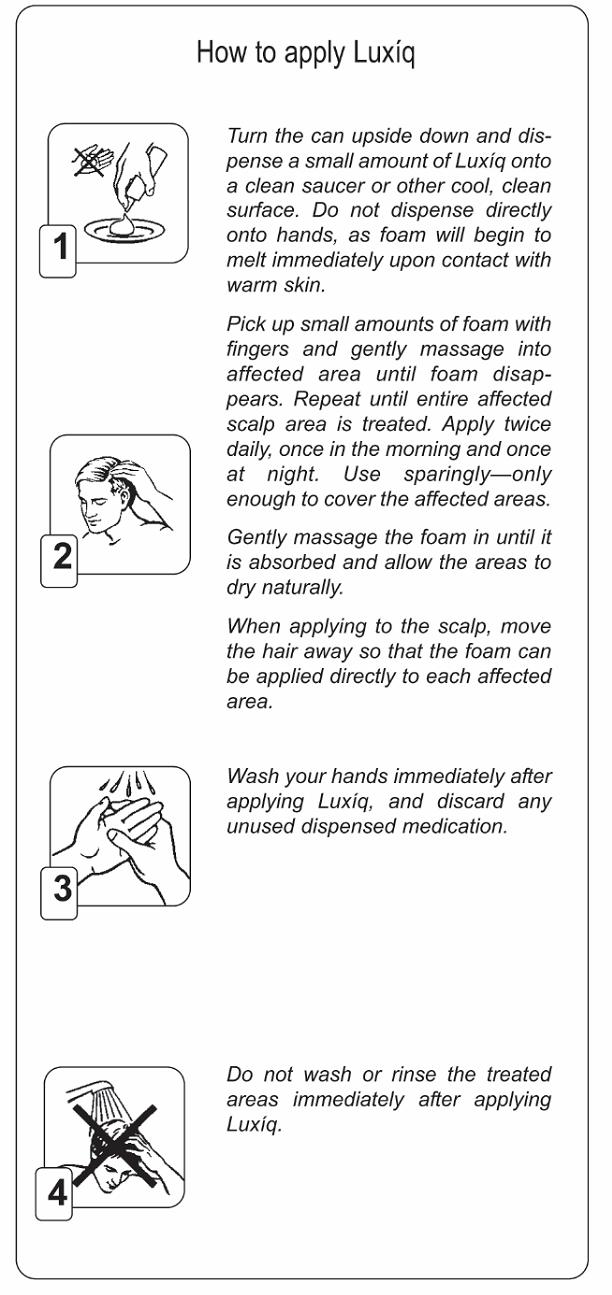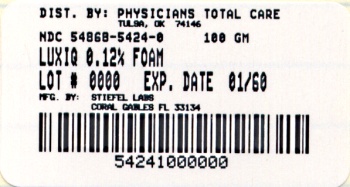 DRUG LABEL: LUXIQ
NDC: 54868-5424 | Form: AEROSOL, FOAM
Manufacturer: Physicians Total Care, Inc.
Category: prescription | Type: HUMAN PRESCRIPTION DRUG LABEL
Date: 20100629

ACTIVE INGREDIENTS: BETAMETHASONE VALERATE 1.2 mg/1 g
INACTIVE INGREDIENTS: CETYL ALCOHOL; CITRIC ACID MONOHYDRATE; ALCOHOL; POLYSORBATE 60; POTASSIUM CITRATE; PROPYLENE GLYCOL; WATER; STEARYL ALCOHOL

Luxíq®
(betamethasone valerate) Foam, 0.12%

Rx Only

For Dermatologic Use Only

Not for Ophthalmic Use

DESCRIPTION

Luxíq Foam contains betamethasone valerate, USP, a synthetic corticosteroid, for topical dermatologic use. The corticosteroids constitute a class of primarily synthetic steroids used topically as anti-inflammatory agents.

Betamethasone valerate is 9-fluoro11ß,17, 21-trihydroxy-16ß-methylpregna-1, 4-diene-3, 20-dione 17-valerate, with the empirical formula C27H37FO6, a molecular weight of 476.58.The following is the chemical structure:

Betamethasone valerate is a white to practically white, odorless crystalline powder, and is practically insoluble in water, freely soluble in acetone and in chloroform, soluble in alcohol, and slightly soluble in benzene and in ether.

Luxíq® (betamethasone valerate) Foam, 0.12%, contains 1.2 mg betamethasone valerate, USP, per gram in a thermolabile hydroethanolic foam vehicle consisting of cetyl alcohol, citric acid, ethanol (60.4%), polysorbate 60, potassium citrate, propylene glycol, purified water, and stearyl alcohol pressurized with a hydrocarbon (propane/butane) propellant.

CLINICAL PHARMACOLOGY

Like other topical corticosteroids, betamethasone valerate foam has anti-inflammatory, antipruritic, and vasoconstrictive properties. The mechanism of the anti-inflammatory activity of the topical steroids, in general, is unclear. However, corticosteroids are thought to act by the induction of phospholipase A2 inhibitory proteins, collectively called lipocortins. It is postulated that these proteins control the biosynthesis of potent mediators of inflammation such as prostaglandins and leukotrienes by inhibiting the release of their common precursor arachidonic acid. Arachidonic acid is released from membrane phospholipids by phospholipase A2.

Pharmacokinetics

Topical corticosteroids can be absorbed from intact healthy skin. The extent of percutaneous absorption of topical corticosteroids is determined by many factors, including the vehicle and the integrity of the epidermal barrier. Occlusion, inflammation and/or other disease processes in the skin may also increase percutaneous absorption.

The use of pharmacodynamic endpoints for assessing the systemic exposure of topical corticosteroids is necessary due to the fact that circulating levels are well below the level of detection. Once absorbed through the skin, topical corticosteroids are handled through pharmacokinetic pathways similar to systemically administered corticosteroids. They are metabolized, primarily in the liver, and are then excreted by the kidneys. In addition, some corticosteroids and their metabolites are also excreted in the bile.

CLINICAL STUDIES

The safety and efficacy of Luxíq has been demonstrated in a four-week trial. An adequate and well-controlled clinical trial was conducted in 190 patients with moderate to severe scalp psoriasis. Patients were treated twice daily for four weeks with Luxíq Foam, Placebo foam, a commercially available betamethasone valerate lotion 0.12% (formerly expressed as 0.1% betamethasone), or Placebo lotion. At four weeks of treatment, study results of 159 patients demonstrated that the efficacy of Luxíq Foam in treating scalp psoriasis is superior to that of Placebo foam, and is comparable to that of a currently marketed BMV lotion (see Table below).

Subjects with Target Lesion Parameter Clear at Endpoint | Luxíq Foam n (%) | BMV lotion n (%) | Placebo foam n (%)
Scaling | 30 (47%) | 22 (35%) | 2 (6%)
Erythema | 26 (41%) | 16 (25%) | 2 (6%)
Plaque Thickness | 42 (66%) | 25 (40%) | 5 (16%)
Investigator's Global: Subjects Completely Clear or Almost Clear at Endpoint | 43 (67%) | 29 (46%) | 6 (19%)

INDICATIONS AND USAGE

Luxíq is a medium potency topical corticosteroid indicated for relief of the inflammatory and pruritic manifestations of corticosteroid-responsive dermatoses of the scalp.

CONTRAINDICATIONS

Luxíq is contraindicated in patients who are hypersensitive to betamethasone valerate, to other corticosteroids, or to any ingredient in this preparation.

PRECAUTIONS

General

Systemic absorption of topical corticosteroids has caused reversible hypothalamic-pituitary-adrenal (HPA) axis suppression with the potential for glucocorticosteroid insufficiency after withdrawal of treatment. Manifestations of Cushing’s syndrome, hyperglycemia, and glucosuria can also be produced in some patients by systemic absorption of topical corticosteroids while on treatment.

Conditions which augment systemic absorption include the application of the more potent steroids, use over large surface areas, prolonged use, and the addition of occlusive dressings.

Therefore, patients applying a topical steroid to a large surface area or to areas under occlusion should be evaluated periodically for evidence of HPA axis suppression. If HPA axis suppression is noted, an attempt should be made to withdraw the drug, to reduce the frequency of application, or to substitute a less potent steroid.

Recovery of HPA axis function is generally prompt upon discontinuation of topical corticosteroids. Infrequently, signs and symptoms of glucocorticosteroid insufficiency may occur requiring supplemental systemic corticosteroids. For information on systemic supplementation, see prescribing information for those products.

Pediatric patients may be more susceptible to systemic toxicity from equivalent doses due to their larger skin surface to body mass ratios. (See PRECAUTIONS-Pediatric Use.)

If irritation develops, Luxíq should be discontinued and appropriate therapy instituted. Allergic contact dermatitis with corticosteroids is usually diagnosed by observing a failure to heal rather than noting a clinical exacerbation, as with most topical products not containing corticosteroids. Such an observation should be corroborated with appropriate diagnostic patch testing.

In the presence of dermatological infections, the use of an appropriate antifungal or antibacterial agent should be instituted. If a favorable response does not occur promptly, use of Luxíq should be discontinued until the infection has been adequately controlled.

Information for Patients

Patients using topical corticosteroids should receive the following information and instructions:

1. This medication is to be used as directed by the physician. It is for external use only. Avoid contact with the eyes.
2. This medication should not be used for any disorder other than that for which it was prescribed.
3. The treated scalp area should not be bandaged or otherwise covered or wrapped so as to be occlusive unless directed by the physician.
4. Patients should report to their physician any signs of local adverse reactions.
5. As with other corticosteroids, therapy should be discontinued when control is achieved. If no improvement is seen within 2 weeks, contact the physician.

Laboratory Tests

The following tests may be helpful in evaluating patients for HPA axis suppression:

ACTH stimulation test

A.M. plasma cortisol test

Urinary free cortisol test

Carcinogenesis, Mutagenesis, and Impairment of Fertility

Long-term animal studies have not been performed to evaluate the carcinogenic potential or the effect on fertility of betamethasone valerate.

Betamethasone was genotoxic in the in vitro human peripheral blood lymphocyte chromosome aberration assay with metabolic activation and in the in vivo mouse bone marrow micronucleus assay.

Pregnancy Category C

Corticosteroids have been shown to be teratogenic in laboratory animals when administered systemically at relatively low dosage levels. Some corticosteroids have been shown to be teratogenic after dermal application in laboratory animals. There are no adequate and well-controlled studies in pregnant women. Therefore, Luxíq should be used during pregnancy only if the potential benefit justifies the potential risk to the fetus.

Drugs of this class should not be used extensively on pregnant patients, in large amounts, or for prolonged periods of time.

Nursing Mothers

Systemically administered corticosteroids appear in human milk and could suppress growth, interfere with endogenous corticosteroid production, or cause other untoward effects. It is not known whether topical administration of corticosteroids could result in sufficient systemic absorption to produce detectable quantities in breast milk. Because many drugs are excreted in human milk, caution should be exercised when Luxíq is administered to a nursing woman.

Pediatric Use

Safety and effectiveness in pediatric patients have not been established. Because of a higher ratio of skin surface area to body mass, pediatric patients are at a greater risk than adults of HPA axis suppression and Cushing’s syndrome when they are treated with topical corticosteroids. They are therefore also at greater risk of adrenal insufficiency during and/or after withdrawal of treatment. Adverse effects including striae have been reported with inappropriate use of topical corticosteroids in infants and children.

Hypothalamic-pituitary-adrenal (HPA) axis suppression, Cushing’s syndrome, linear growth retardation, delayed weight gain, and intracranial hypertension have been reported in children receiving topical corticosteroids. Manifestations of adrenal suppression in children include low plasma cortisol levels and an absence of response to ACTH stimulation. Manifestations of intracranial hypertension include bulging fontanelles, headaches, and bilateral papilledema.

Administration of topical corticosteroids to children should be limited to the least amount compatible with an effective therapeutic regimen. Chronic corticosteroid therapy may interfere with the growth and development of children.

ADVERSE REACTIONS

The most frequent adverse event was burning/itching/stinging at the application site; the incidence and severity of this event were as follows:

Incidence and severity of burning/itching/stinging
 |  | Maximum severity
Product | Total incidence | Mild | Moderate | Severe
Product | Total incidence | Mild | Moderate
Luxíq Foam n=63 | 34 (54%) | 28 (44%) | 5 (8%) | 1 (2%)
Betamethasone valerate lotion n=63 | 33 (52%) | 26 (41%) | 6 (10%) | 1 (2%)
Betamethasone valerate lotion n=63 | 33 (52%) | 26 (41%) | 6 (10%)
Placebo Foam n=32 | 24 (75%) | 13 (41%) | 7 (22%) | 4 (12%)
Placebo Lotion n=30 | 20 (67%) | 12 (40%) | 5 (17%) | 3 (10%)

Other adverse events which were considered to be possibly, probably, or definitely related to Luxíq occurred in 1 patient each; these were paresthesia, pruritus, acne, alopecia, and conjunctivitis.

The following additional local adverse reactions have been reported with topical corticosteroids, and they may occur more frequently with the use of occlusive dressings. These reactions are listed in an approximately decreasing order of occurrence: irritation; dryness; folliculitis; acneiform eruptions; hypopigmentation; perioral dermatitis; allergic contact dermatitis; secondary infection; skin atrophy; striae; and miliaria.

Systemic absorption of topical corticosteroids has produced reversible hypothalamic-pituitary-adrenal (HPA) axis suppression, manifestations of Cushing’s syndrome, hyperglycemia, and glucosuria in some patients.

OVERDOSAGE

Topically applied Luxíq can be absorbed in sufficient amounts to produce systemic effects. (See PRECAUTIONS)

DOSAGE AND ADMINISTRATION

Note: For proper dispensing of foam, can must be inverted.

For application to the scalp invert can and dispense a small amount of Luxíq onto a saucer or other cool surface. Do not dispense directly onto hands as foam will begin to melt immediately upon contact with warm skin. Pick up small amounts of foam with fingers and gently massage into affected area until foam disappears. Repeat until entire affected scalp area is treated. Apply twice daily, once in the morning and once at night.

As with other corticosteroids, therapy should be discontinued when control is achieved. If no improvement is seen within 2 weeks, reassessment of the diagnosis may be necessary.

Luxíq should not be used with occlusive dressings unless directed by a physician.

HOW SUPPLIED

Luxíq is supplied in aluminum cans of:

100 gram | NDC 54868-5424-0

Store at controlled room temperature 68–77°F (20–25°C).

WARNING

FLAMMABLE. AVOID FIRE, FLAME OR SMOKING DURING AND IMMEDIATELY FOLLOWING APPLICATION. Keep out of reach of children. Contents under pressure. Do not puncture or incinerate container. Do not expose to heat or store at temperatures above 120°F (49°C).

Manufactured for

Stiefel Laboratories, Inc.

Coral Gables, FL 33134

USA

For additional information visit www.luxiq.com

Questions? Call 1-888-500-DERM (3376). Side effects may be reported to this number.

303203

P/N: xxxxxxxx

Lixuq, VersaFoam-HF, VersaFoam-HF & Design, Stiefel, and Stiefel & Design are registered trademarks of Stiefel Laboratories, Inc.

©2009 Stiefel Laboratories, Inc.

Relabeling of "Additional" barcode label by:
Physicians Total Care, Inc.
Tulsa, OK 74146

PATIENT INFORMATION

Luxíq®

(betamethasone valerate) Foam, 0.12%

About Luxíq

Your doctor has prescribed Luxíq (betamethasone valerate) Foam, 0.12%, for the relief of corticosteroid-responsive skin conditions of the scalp. Luxíq works because its active ingredient is betamethasone valerate, 0.12%. Betamethasone belongs to a group of medicines known as topical corticosteroids. These agents are used to reduce the inflammation, redness, swelling, itching, and tenderness associated with dermatologic conditions.

Other ingredients in Luxíq include cetyl alcohol, citric acid, ethanol, polysorbate 60, potassium citrate, propylene glycol, purified water, and stearyl alcohol. The foam is dispensed from an aluminum can that is pressurized by a hyrdrocarbon propellant (propane and butane).

If you answer YES to one or more of the following questions, tell your doctor (or pharmacist) before using this medicine, so you can get advice about what to do.

- Are you allergic to any of the ingredients contained in Luxíq?
- Are you pregnant? Planning on becoming pregnant while using Luxíq? Or are you breastfeeding?
- Do you think you have an infection on your scalp?

- Do not use this medication for any condition other than the one for which it was prescribed.
- Luxíq is for external use only.
- Keep the foam away from your eyes, as it will sting. If the foam gets into your eyes, rinse well with cold water. If the stinging continues, contact your doctor immediately.

WHAT YOU SHOULD KNOW ABOUT LUXÍQ:

What to do if you miss an application

If you forget to apply Luxíq at the scheduled time, use it as soon as you remember, and then go back to your regular schedule. If you remember at or about the time of your next daily application, apply that dose and continue with your normal application schedule. If you miss several doses, tell your doctor at your next appointment.

About side effects

As with all medications, there may be some side effects. The most frequent side effects associated with the use of Luxíq include mild burning, stinging, or itching at the site of application. These side effects typically disappear shortly after application.

Let your doctor know if you notice any of the following:

- Any unusual effects that you do not understand.
- Affected areas that do not seem to be healing after several weeks of using the foam.

Important safety notes

- The treated areas should not be bandaged or covered unless directed by your doctor.
- Keep this and all medicines out of the reach of children.
- Store the can at controlled room temperature 68-77oF (20-25oC) and protect it from direct sunlight, as this is a pressurized container.
- Keep away from and do not spray near fire, open flame, or direct heat--this product is flammable. Do not smoke while using or holding the can. Keep the can away from all sources of ignition. Do not pierce or burn the can, and never throw the can in a fire, even if empty.
- When you have finished your treatment, dispose of the can safely. A completely empty can is recyclable.
- Do not use the foam after the expiration date shown on the bottom of the can.
- Do not give Luxíq to anyone else. Your doctor has prescribed this medicine for your use only.

Manufactured for

Stiefel Laboratories, Inc.

Coral Gables, FL 33134

USA

For additional information visit www.luxiq.com

Questions? Call 1-888-500-DERM (3376), Serious side effects may be reported to this number.

303203

P/N: xxxxxxxx

Printed in: U.S.A.

November 2009

Luxiq, VersaFoam-HF, VErsaFoam-HF & Design, Stiefel, and Stiefel & Design are registered trademarks of Stiefel Laboratories, Inc.

©2009 Stiefel Laboratories, Inc.

PACKAGE LABEL

Principal Display Panel

NDC 54868-5424-0

Luxiq®

(betamethasone valerate)

Foam, 0.12%

100g

Rx only

CFC FREE

DELIVERED IN VersaFoam-HFTM

HYDROETHANOLIC FORMULATION